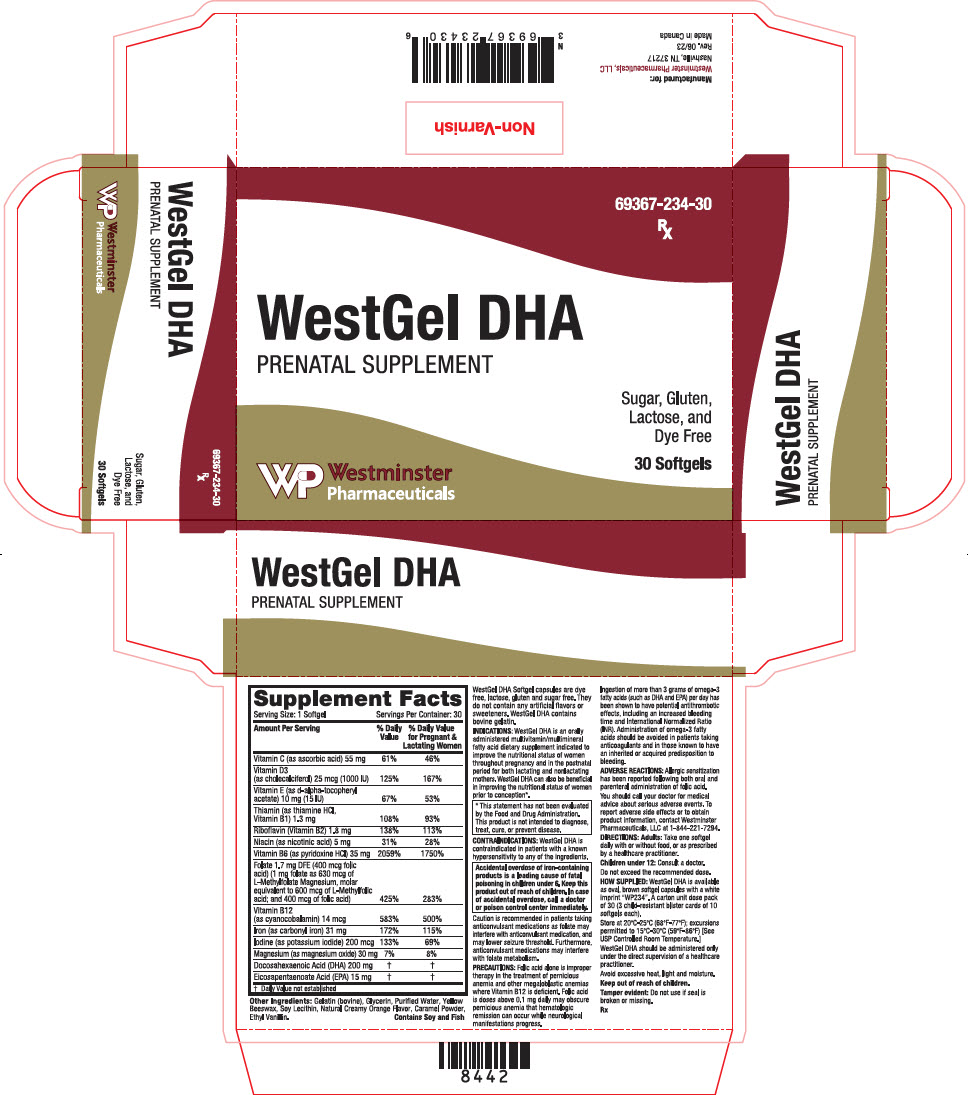 DRUG LABEL: WestGel DHA
NDC: 69367-234 | Form: CAPSULE, LIQUID FILLED
Manufacturer: Westminster Pharmaceuticals, LLC
Category: other | Type: DIETARY SUPPLEMENT
Date: 20230714

ACTIVE INGREDIENTS: ASCORBIC ACID 55 mg/1 1; CHOLECALCIFEROL 1000 [iU]/1 1; .ALPHA.-TOCOPHEROL ACETATE, D- 15 [iU]/1 1; THIAMINE HYDROCHLORIDE 1.3 mg/1 1; RIBOFLAVIN 1.8 mg/1 1; NIACIN 5 mg/1 1; PYRIDOXINE HYDROCHLORIDE 35 mg/1 1; LEVOMEFOLATE MAGNESIUM 600 ug/1 1; FOLIC ACID 400 ug/1 1; CYANOCOBALAMIN 14 ug/1 1; IRON PENTACARBONYL 31 mg/1 1; POTASSIUM IODIDE 200 ug/1 1; MAGNESIUM OXIDE 30 mg/1 1; DOCONEXENT 200 mg/1 1; ICOSAPENT 15 mg/1 1
INACTIVE INGREDIENTS: GELATIN, UNSPECIFIED; GLYCERIN; WATER; CARAMEL; ETHYL VANILLIN; YELLOW WAX; LECITHIN, SOYBEAN; ORANGE

WestGel DHA

STATEMENT OF IDENTITY

Supplement Facts
Serving Size: 1 Softgel | Servings Per Container: 30
Amount Per Serving | % Daily Value | % Daily Value for Pregnant & Lactating Women
Vitamin C (as ascorbic acid) 55 mg | 61% | 46%
Vitamin D3 (as cholecalciferol) 25 mcg (1000 IU) | 125% | 167%
Vitamin E (as d-alpha-tocopheryl acetate) 10 mg (15 IU) | 67% | 53%
Thiamin (as thiamine HCl, Vitamin B1) 1.3 mg | 108% | 93%
Riboflavin (Vitamin B2) 1.8 mg | 138% | 113%
Niacin (as nicotinic acid) 5 mg | 31% | 28%
Vitamin B6 (as pyridoxine HCl) 35 mg | 2059% | 1750%
Folate 1.7 mg DFE (400 mcg folic acid) (1 mg folate as 630 mcg of L-Methylfolate Magnesium, molar equivalent to 600 mcg of L-Methylfolic acid; and 400 mcg of folic acid) | 425% | 283%
Vitamin B12 (as cyanocobalamin) 14 mcg | 583% | 500%
Iron (as carbonyl iron) 31 mg | 172% | 115%
Iodine (as potassium iodide) 200 mcg | 133% | 69%
Magnesium (as magnesium oxide) 30 mg | 7% | 8%
Docosahexaenoic Acid (DHA) 200 mg | [Daily Value not established]
Eicosapentaenoate Acid (EPA) 15 mg

Other Ingredients: Gelatin (bovine), Glycerin, Purified Water, Yellow Beeswax, Soy Lecithin, Natural Creamy Orange Flavor, Caramel Powder, Ethyl Vanillin.

Contains Soy and Fish

WestGel DHA Softgel capsules are dye free, lactose, gluten and sugar free. They do not contain any artificial flavors or sweeteners. WestGel DHA contains bovine gelatin.

INDICATIONS

WestGel DHA is an orally administered multivitamin/multimineral fatty acid dietary supplement indicated to improve the nutritional status of women throughout pregnancy and in the postnatal period for both lactating and nonlactating mothers. WestGel DHA can also be beneficial in improving the nutritional status of women prior to conception [This statement has not been evaluated by the Food and Drug Administration. This product is not intended to diagnose, treat, cure, or prevent disease.] .

CONTRAINDICATIONS

WestGel DHA is contraindicated in patients with a known hypersensitivity to any of the ingredients.

Accidental overdose of iron-containing products is a leading cause of fatal poisoning in children under 6. Keep this product out of reach of children. In case of accidental overdose, call a doctor or poison control center immediately.

Caution is recommended in patients taking anticonvulsant medications as folate may interfere with anticonvulsant medication, and may lower seizure threshold. Furthermore, anticonvulsant medications may interfere with folate metabolism.

PRECAUTIONS

Folic acid alone is improper therapy in the treatment of pernicious anemia and other megaloblastic anemias where Vitamin B12 is deficient. Folic acid is doses above 0.1 mg daily may obscure pernicious anemia that hematologic remission can occur while neurological manifestations progress.

Ingestion of more than 3 grams of omega-3 fatty acids (such as DHA and EPA) per day has been shown to have potential antithrombotic effects, including an increased bleeding time and International Normalized Ratio (INR). Administration of omega-3 fatty acids should be avoided in patients taking anticoagulants and in those known to have an inherited or acquired predisposition to bleeding.

ADVERSE REACTIONS

Allergic sensitization has been reported following both oral and parenteral administration of folic acid. You should call your doctor for medical advice about serious adverse events. To report adverse side effects or to obtain product information, contact Westminster Pharmaceuticals, LLC at 1-844-221-7294.

DIRECTIONS

Adults

Take one softgel daily with or without food, or as prescribed by a healthcare practitioner.

Children under 12

Consult a doctor. Do not exceed the recommended dose.

HOW SUPPLIED

WestGel DHA is available as oval, brown softgel capsules with a white imprint "WP234". A carton unit dose pack of 30 (3 child-resistant blister cards of 10 softgels each).

Store at 20ºC-25ºC (68ºF-77ºF); excursions permitted to 15ºC-30ºC (59ºF-86ºF) [See USP Controlled Room Temperature.]

WestGel DHA should be administered only under the direct supervision of a healthcare practitioner.

Avoid excessive heat, light and moisture.

Keep out of reach of children.

Tamper evident: Do not use if seal is broken or missing.

HEALTH CLAIM

Rx

PRINCIPAL DISPLAY PANEL - 30 Softgel Blister Pack Carton

69367-234-30
Rx

WestGel DHA
PRENATAL SUPPLEMENT

Sugar, Gluten,
Lactose, and
Dye Free

30 Softgels

Westminster
Pharmaceuticals